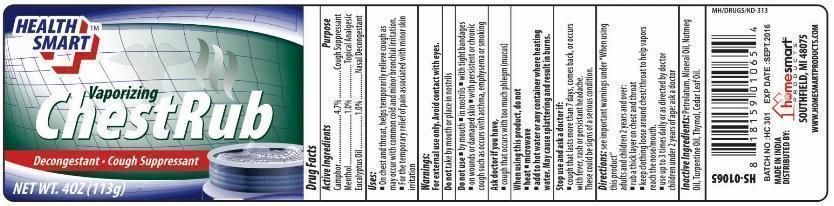 DRUG LABEL: Health Smart Vaporizing Chest Rub
NDC: 52862-902 | Form: GEL
Manufacturer: International Wholesale Inc
Category: otc | Type: HUMAN OTC DRUG LABEL
Date: 20250710

ACTIVE INGREDIENTS: CAMPHOR (SYNTHETIC) 4.7 g/100 g; MENTHOL 1 g/100 g; EUCALYPTUS OIL 1 g/100 g
INACTIVE INGREDIENTS: CEDAR LEAF OIL; NUTMEG OIL; MINERAL OIL; PETROLATUM; THYMOL; TURPENTINE OIL

Health Smart Vapourising Chest Rub

Active Ingredients

Camphor 4.7%

Menthol 1.0%

Eucalyptus Oil 1.0%

Purpose

Cough Suppressant

Topical Analgesic

Nasal Decongestant

Uses

- On chest and throat, helps temporarily relieve cough as may occur with common cold and minor bronchial irritation.
- For the temporary relief of pain associated with minor skin irritation.

Warnings

For external use only. Avoid contact with eyes.

Do not take by mouth or place in nostrils.

Do not use

- by mouth
- in nostrils
- with tight bandages
- on wounds or damaged skin
- with persistent or chronic cough such as occurs with asthma, emphysema or smoking

Ask doctor if you have,

- cough that occurs with too much phlegm (mucus)

When using this product, do not

- heat
- microwave
- add to hot water or any container where heating water. May cause splattering and result in burns

Stop use and ask a doctor if:

- cough that lasts more than 7 days, comes back, or occurs with fever, rash or persistent headache. These could be signs of a serious conditions

Keep out of the reach of children

If ingested get medical help or contact a Poison control center immediately

DOSAGE AND ADMINISTRATION

Directions: see important warnings under “When using this product”

adults and children 2 years and over:

- rub a thick layer on chest and throat
- keep clothing loose around chest/throat to help vapors reach the nose/mouth
- use up to 3 times daily as directed by doctor

children under 2 years of age: ask a doctor

Inactive Ingredients

Petrolatum, Mineral Oil, Nutmeg Oil, Turpentine Oil, Thymol, Cedar Leaf Oil

PRINCIPAL DISPLAY PANEL

HEALTH SMART VAPORISING CHEST RUB GEL

DECONGESTANT AND COUGH SUPPRESSANT

NET WT.4 OZ (113g)